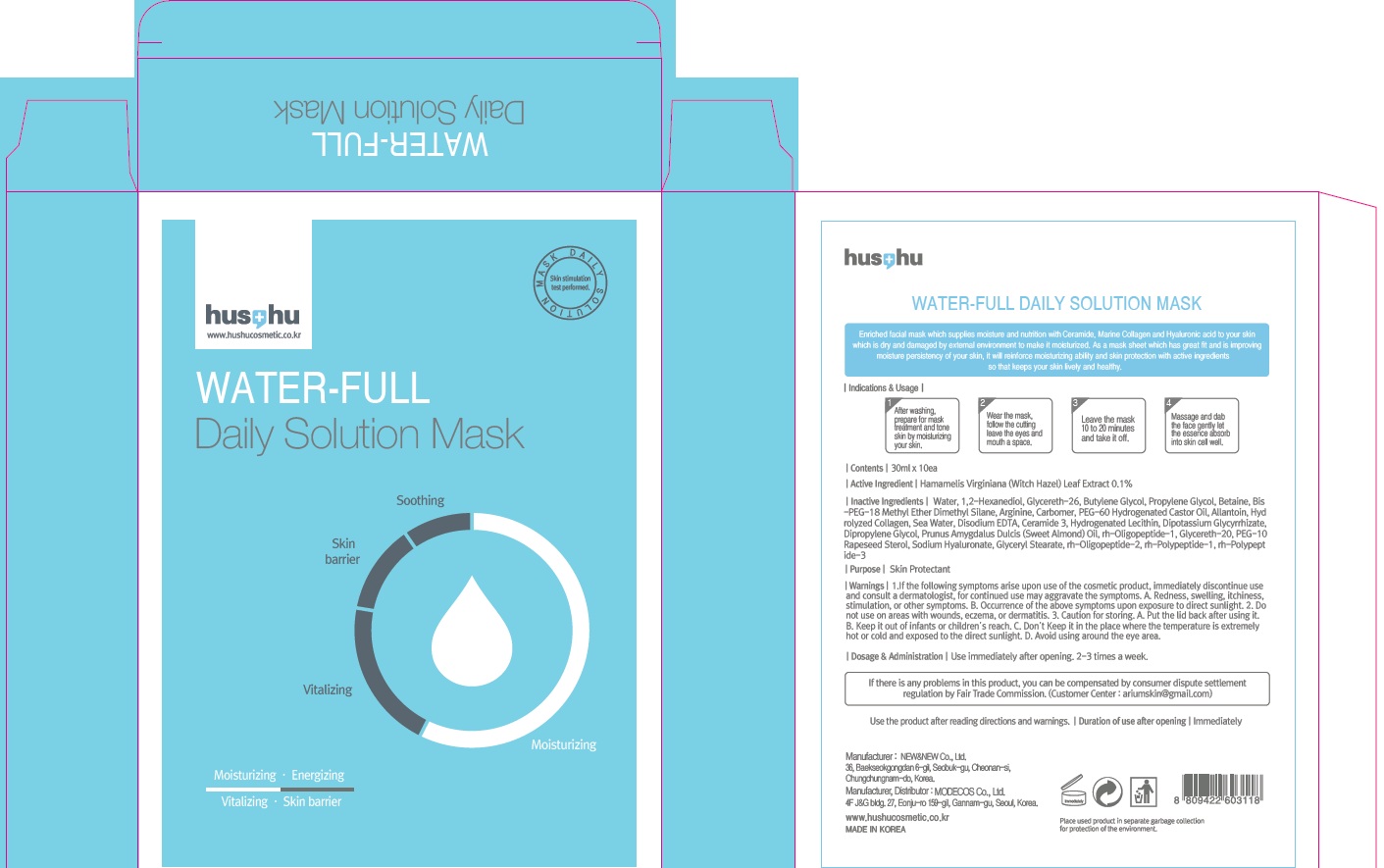 DRUG LABEL: Water Full Daily Mask
NDC: 70566-020 | Form: SOLUTION
Manufacturer: MODECOS CO., LTD.
Category: otc | Type: HUMAN OTC DRUG LABEL
Date: 20160329

ACTIVE INGREDIENTS: Witch Hazel 0.03 g/10 1
INACTIVE INGREDIENTS: Water; 1,2-Hexanediol

ACTIVE INGREDIENT

Active Ingredient: Hamamelis Virginiana (Witch Hazel) Leaf Extract 0.1%

INACTIVE INGREDIENT

Inactive Ingredients: Water, 1,2-Hexanediol, Glycereth-26, Butylene Glycol, Propylene Glycol, Betaine, Bis-PEG-18 Methyl Ether Dimethyl Silane, Arginine, Carbomer, PEG-60 Hydrogenated Castor Oil, Allantoin, Hydrolyzed Collagen, Sea Water, Disodium EDTA, Ceramide 3, Hydrogenated Lecithin, Dipotassium Glycyrrhizate, Dipropylene Glycol, Prunus Amygdalus Dulcis (Sweet Almond) Oil, rh-Oligopeptide-1, Glycereth-20, PEG-10 Rapeseed Sterol, Sodium Hyaluronate, Glyceryl Stearate, rh-Oligopeptide-2, rh-Polypeptide-1, rh-Polypeptide-3

PURPOSE

Purpose: Skin Protectant

WARNINGS

Warnings: 1. If the following symptoms arise upon use of the cosmetic product, immediately discontinue use and consult a dermatologist, for continued use may aggravate the symptoms. A. Redness, swelling, itchiness, stimulation, or other symptoms B. Occurrence of the above symptoms upon exposure to direct sunlight. 2. Do not use on areas with wounds, eczema, or dermatitis. 3. Caution for storing. A. Put the lid back after using it. B. Keep it out of infants or children’s reach C. Don’t Keep it in the place where the temperature is extremely hot or cold and exposed to the direct sunlight D. Avoid using around the eye area.

KEEP OUT OF REACH OF CHILDREN

Keep it out of infants or children’s reach

INDICATIONS & USAGE

Indications & Usage: 1. After washing, prepare for mask treatment and tone skin by moisturizing your skin 2. Wear the mask, follow the cutting leave the eyes and mouth a space 3. Leave the mask 10 to 20 minutes and take it off. 4. Massage and dab the face gently let the essence absorb into skin cell well.

DOSAGE & ADMINISTRATION

Dosage & Administration: Use immediately after opening. 2-3 times a week.